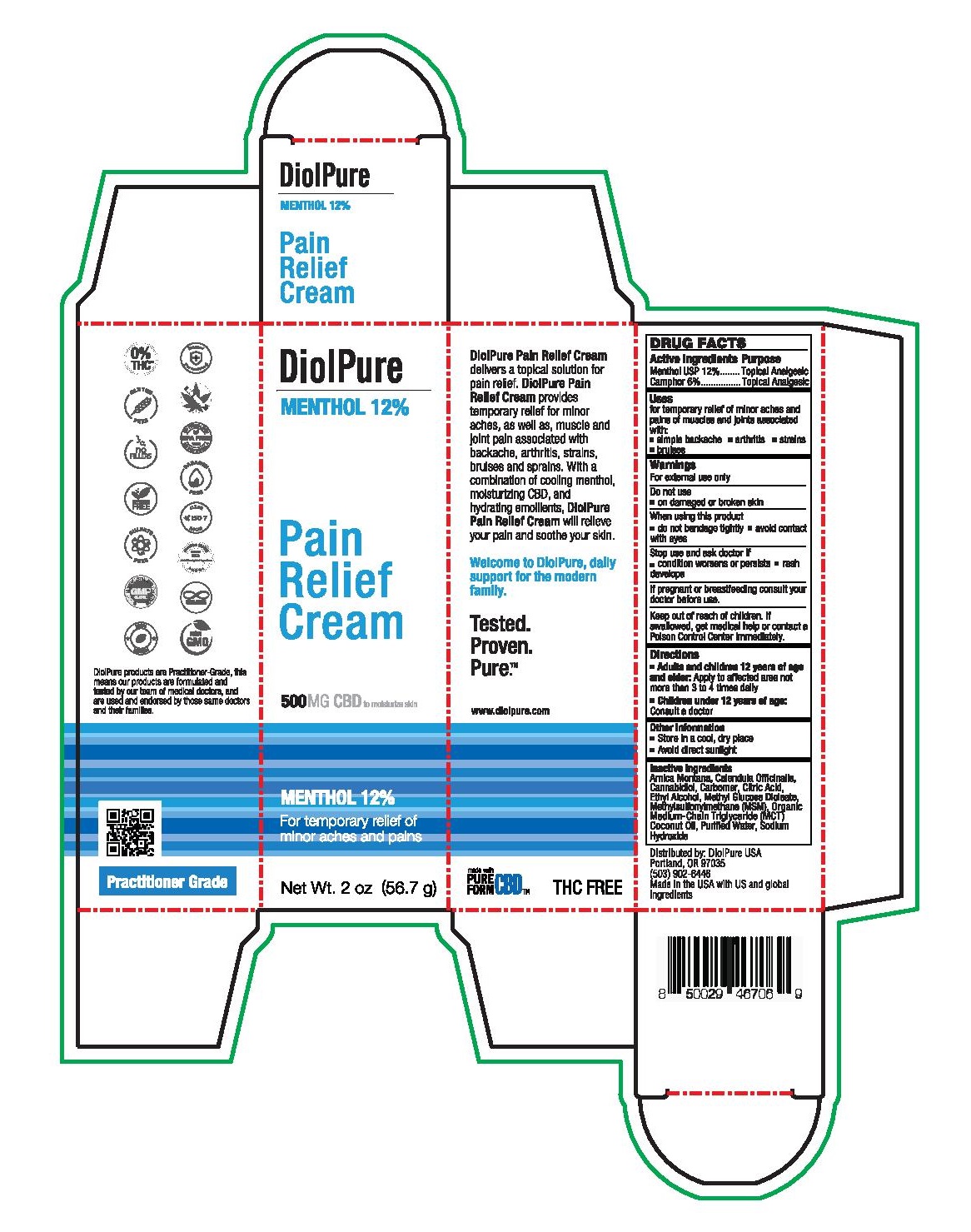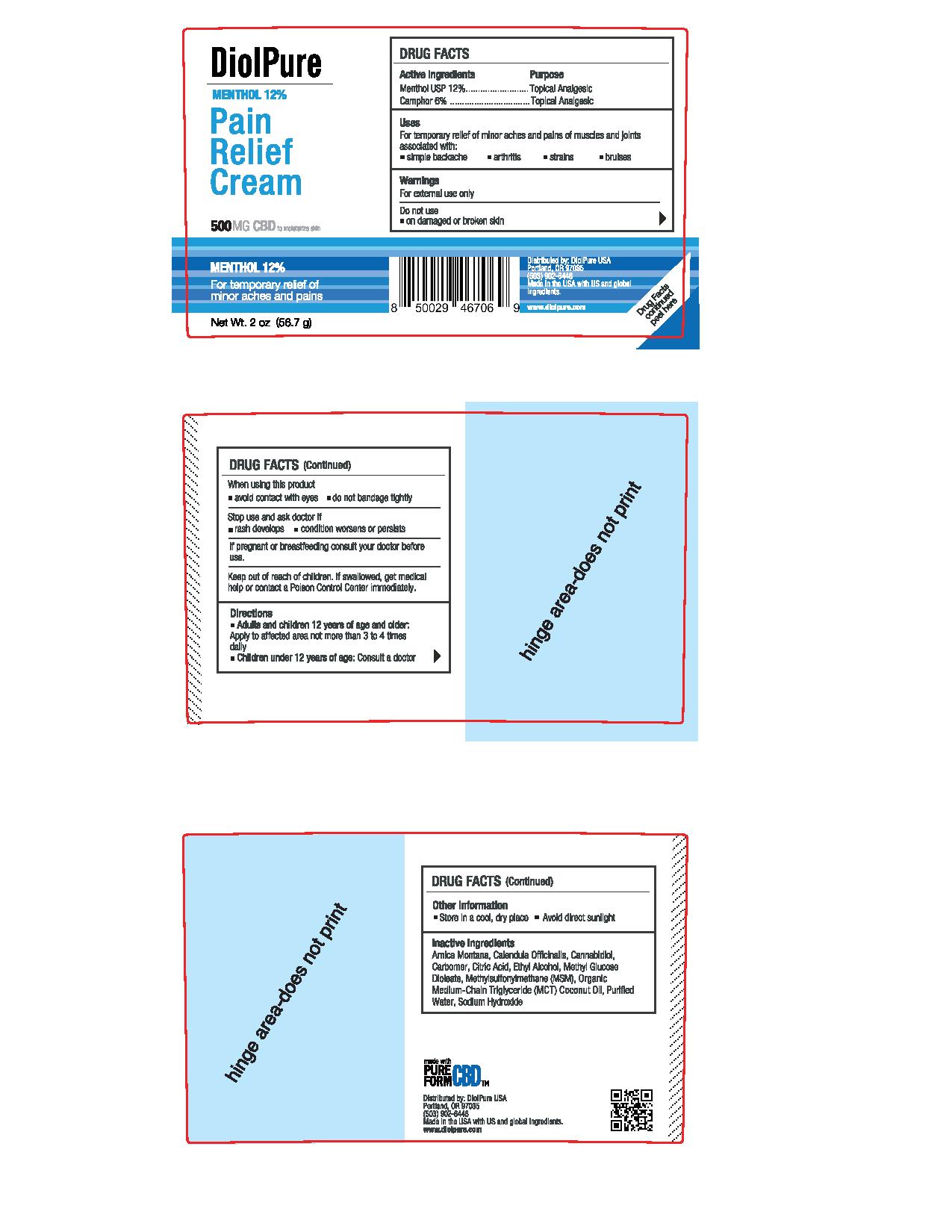 DRUG LABEL: DiolPure Menthol Pain Relief Cream
NDC: 82093-001 | Form: CREAM
Manufacturer: DiolPure, LLC
Category: otc | Type: HUMAN OTC DRUG LABEL
Date: 20210709

ACTIVE INGREDIENTS: CAMPHOR (SYNTHETIC) 6 g/100 g; MENTHOL 12 g/100 g
INACTIVE INGREDIENTS: CANNABIDIOL; CALENDULA OFFICINALIS FLOWERING TOP; DIMETHYL SULFONE; SODIUM HYDROXIDE; CITRIC ACID MONOHYDRATE; CARBOMER HOMOPOLYMER, UNSPECIFIED TYPE; ALCOHOL; METHYL GLUCOSE DIOLEATE; MEDIUM-CHAIN TRIGLYCERIDES; ARNICA MONTANA; WATER; COCONUT OIL

DiolPure Menthol Pain Relief Cream

Active ingredients

Menthol USP 12%

Camphor 6%

Purpose

Menthol USP 12%.....................Topical Analgesic

Camphor 6%.............................Topical Analgesic

Uses

for temporary relief of minor aches and pains of muscles and joints associated with:

- simple backache
- arthritis
- strains
- bruises

Warnings

For external use only

Do not use

- on damaged or broken skin

When using this product

- do not bandage tightly
- avoid contact with eyes

Stop use and ask doctor if

- condition worses or persists
- rash develops

PREGNANCY OR BREAST FEEDING

If pregnant or breastfeeding consult your doctor before use.

Keep out of reach of children. If swallowed, get medical help or contact a Poison Control Center immediately.

Directions

- Adults and children 12 years of age and older: Apply to affected area not more than 3 to 4 times daily
- Children under 12 years of age: Consult a doctor

Other information

- Store in a cool, dry place
- Avoid direct sunlight

Inactive ingredients

Arnica Montana, Calendula Officinalis, Cannabidiol, Carbomer, Citric Acid, Ethyl Alcohol, Methyl Glucose Dioleate, Methylsulfonylmethane (MSM), Organic Medium-Chain Triglyceride (MCT), Coconut Oil, Purified Water, Sodium Hydroxide

PACKAGE LABEL

DiolPure

Menthol 12%

Pain Relief Cream

500MG CBD to moisturize skin

Menthol 12%

For temporary relief of minor aches and pains

Net Wt. 2 oz (56.7 g)